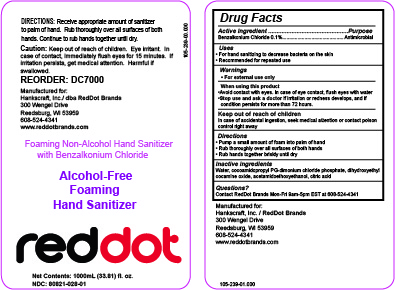 DRUG LABEL: Reddot Hand Sanitizer
NDC: 80821-028 | Form: LIQUID
Manufacturer: A J S & Associates, Inc
Category: otc | Type: HUMAN OTC DRUG LABEL
Date: 20211216

ACTIVE INGREDIENTS: BENZALKONIUM CHLORIDE 1 mg/1 mL
INACTIVE INGREDIENTS: CITRIC ACID MONOHYDRATE 1 mL/1 mL; WATER 1 mL/1 mL; COCAMIDOPROPYL PG-DIMONIUM CHLORIDE PHOSPHATE 1 mL/1 mL; ACETAMIDOETHOXYETHANOL 1 mL/1 mL; DIHYDROXYETHYL COCAMINE OXIDE 1 mL/1 mL

Directions

- Receive appropriate amount of sanitizer to palm of hand.
- Rub thoroughly over all surfaces of both hands.
- Continue to rub hands together until dry.

Keep out of reach of children. Eye irritant. In case of contact, immediately flush eyes for 15 minutes. If irritation persists, get medical attention. Harmful if swallowed.

Active Ingredient(s)

Benzalkonium Chloride 0.1% . . . . . . . . . Antimicrobial

Use

Recommended for repeated use

Purpose

For hand sanitizing to decrease bacteria on the skin

Recommended for repeated use

Warnings

For external use only.

When using this product:

- Avoid contact with eyes. In case of eye contact, flush eyes with water
- Stop use and ask a doctor if irritation or redness develops, and if condition persists for more than 72 hours.

Keep out of reach of children

In case of accidental ingestion, seek medical attention or contact poison control right away

Directions

- Pump a small amount of foam into palm of hand
- Rub thoroughly over all surfaces of both hands
- Rub hands together briskly until dry

Inactive ingredients

Water, cocoamidopropyl PG-dimonium chloride phosphate, dihydroxyethyl cocamine oxide, acetamidoethoxyethanol, citric acid

Questions

Contact RedDot Brands Mon-Fri 9am-5pm EST at 608-524-4341

Package Label - Principal Display Panel

REORDER: DC7000

Manufactured for:

Hankscraft, Inc./ dba RedDot Brands

300 Wengel Drive

Reedsburg, WI 53959

608-524-4341

www.reddotbrands.com

Foaming Non-Alcohol Hand Sanitizer

with Benzalkonium Chloride

Alcohol-Free

Foaming

Hand Sanitizer

reddot

Net Contents: 1000 mL NDC: 80821-028-01